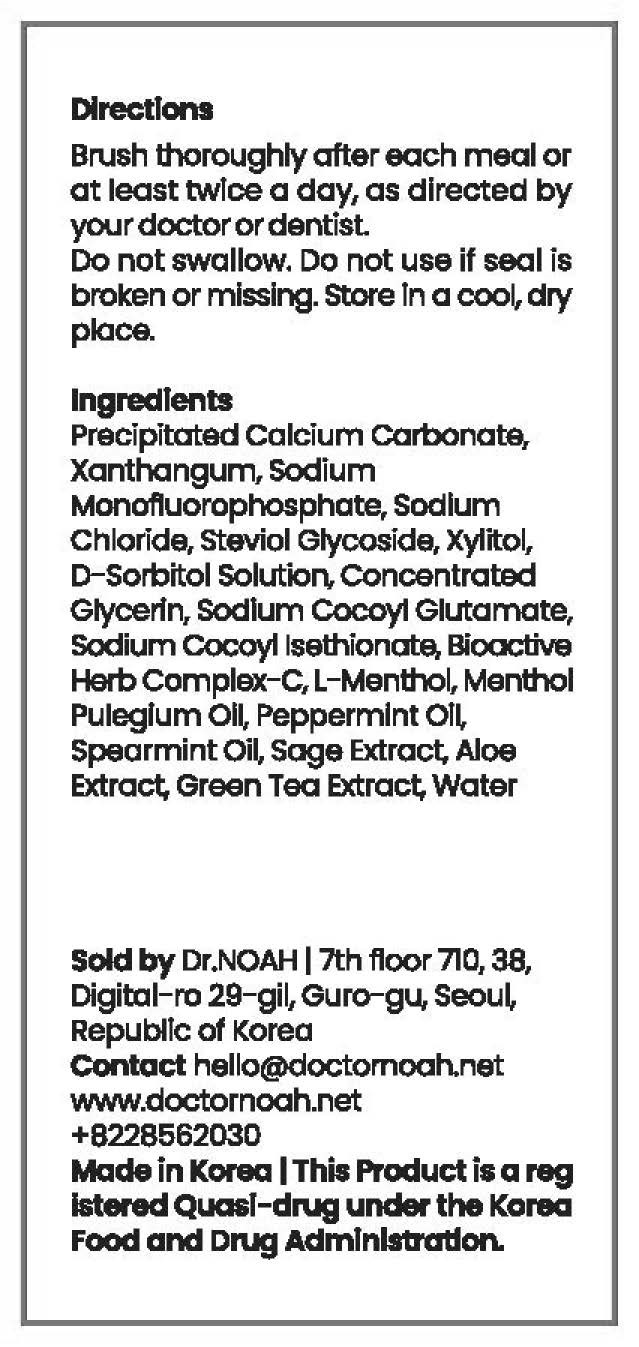 DRUG LABEL: Dr.NOAH MARUFTOOTHPASTE
NDC: 82359-0001 | Form: PASTE
Manufacturer: DR.Noah
Category: otc | Type: HUMAN OTC DRUG LABEL
Date: 20211029

ACTIVE INGREDIENTS: SODIUM MONOFLUOROPHOSPHATE 0.22 g/100 g
INACTIVE INGREDIENTS: SODIUM CHLORIDE; SORBITOL

ACTIVE INGREDIENT

Sodium Fluoride

INACTIVE INGREDIENT

Precipitated Calcium Carbonate
Xanthangum
Sodium Chloride
Steviol Glycoside
Xylitol
D-Sorbitol Solution
Concentrated Glycerin
Sodium Cocoyl Glutamate
Sodium Cocoyl Isethionate
Bioactive Herb Complex-C
L-Menthol
Menthol Pulegium Oil
Peppermint Oil
Spearmint Oil
Sage Extract
Aloe Extract
Green Tea Extract
Water

PURPOSE

■ Keeps teeth white and strong

■ Keep the oral cavity clean

■ Prevents tooth decay and bad breath caused by fluoride

■ Removing plaque, preventing gingivitis and periodontitis

■ Periodontal Disease Prevention

■ Gum Disease Prevention

KEEP OUT OF REACH OF CHILDREN

WARNING

For oral use only
When using this product

■ This toothpaste has a 1,000 ppm fluoride content

■ Do not use other than brushing teeth and be careful not to swallow

Keep out of reach of children

■ if swallowed, seek medical help or contact the poison control center immediately

USES

for oral use only

INDICATION & USAGE SECTION

Brush thoroughly ofter each meal or at least twice a day, as directed by yourdoctorordendst
Do not swallow.

Do not use if seal is broken or missing.

store in a cool, dry place.